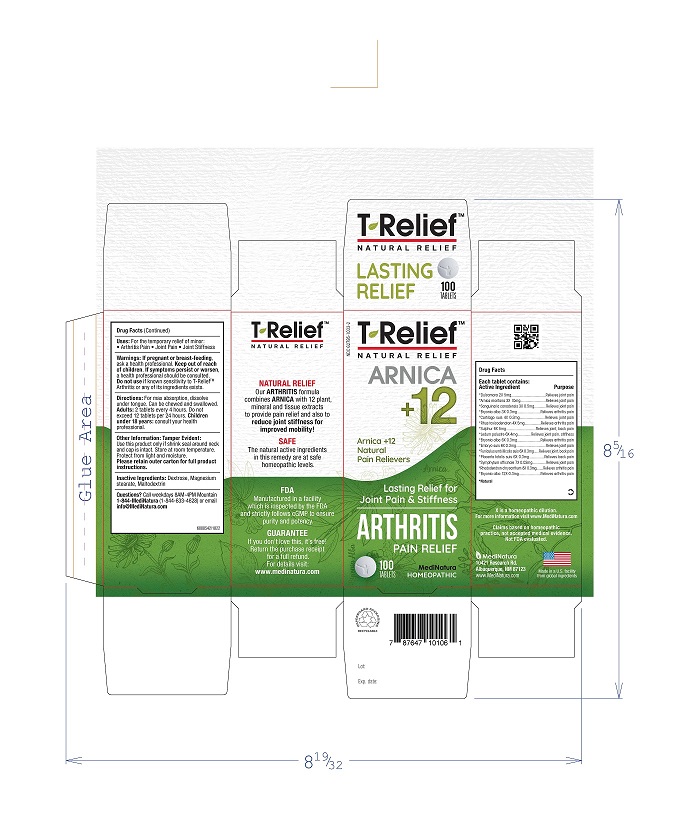 DRUG LABEL: T Relief Arthritis
NDC: 62795-1033 | Form: TABLET
Manufacturer: MediNatura Inc
Category: homeopathic | Type: HUMAN OTC DRUG LABEL
Date: 20230807

ACTIVE INGREDIENTS: ARNICA MONTANA 3 [hp_X]/1 1; BRYONIA ALBA ROOT 3 [hp_X]/1 1; SUS SCROFA CARTILAGE 4 [hp_X]/1 1; SOLANUM DULCAMARA TOP 2 [hp_X]/1 1; SUS SCROFA EMBRYO 6 [hp_X]/1 1; SUS SCROFA UMBILICAL CORD 6 [hp_X]/1 1; LEDUM PALUSTRE TWIG 6 [hp_X]/1 1; SUS SCROFA PLACENTA 6 [hp_X]/1 1; RHODODENDRON AUREUM LEAF 8 [hp_X]/1 1; TOXICODENDRON PUBESCENS LEAF 4 [hp_X]/1 1; SANGUINARIA CANADENSIS ROOT 3 [hp_X]/1 1; SULFUR 6 [hp_X]/1 1; COMFREY ROOT 7 [hp_X]/1 1
INACTIVE INGREDIENTS: MAGNESIUM STEARATE; DEXTROSE; MALTODEXTRIN

T Relief Arthritis Tablet

KEEP OUT OF REACH OF CHILDREN

WARNINGS

Warnings: If pregnant or breatfeeding, ask health proffessional. Keep out of reach of children. If symptoms persist or worsen, a health professional should be consulted. Do not use if known sensitivity to T-Relief™ Arthritis or any of its ingredients exists.

ACTIVE INGREDIENTS

Each tablet contains: *Dulcamara
2X 5mg, *Arnica montana 3X 10mg, *Sanguinaria
canadensis 3X 0.5mg,*Bryonia alba 3X 0.3mg, *Cartilago
suis 4X 0.3mg,*Rhus toxicodendron 4X 5mg, *Sulphur
6X 5mg,*Ledum palustre 6X 4mg,*Bryonia alba 6X
0.3mg, *Embryo suis 6X 0.3mg,*Funiculus umbilicalis
suis 6X 0.3mg, *Placenta totalis suis 6X 0.3mg,
*Symphytum officinale 7X 0.02mg, *Rhododendron
chrysanthum 8X 0.3mg, *Bryonia alba 12X 0.3mg.
*Natural Ingredient

Uses

Relieves

- Arthritis pain
- Joint pain
- Joint stiffness

INACTIVE INGREDIENTS

Inactive Ingredients: Dextrose, Maltodextrin Magnesium stearate.

PURPOSE

Uses: For the temporary relief of minor: Arthritis pain, Joint pain, Joint stiffness

Directions

For max absorption, dissolve under tongue. Can be chewed and swallowed. Adults 2 tablets every 4 hours. Do not exceed 12 tablets per 24 hours. Children under 18 years, consult your health professional.

PACKAGE LABEL

Add image transcription here...